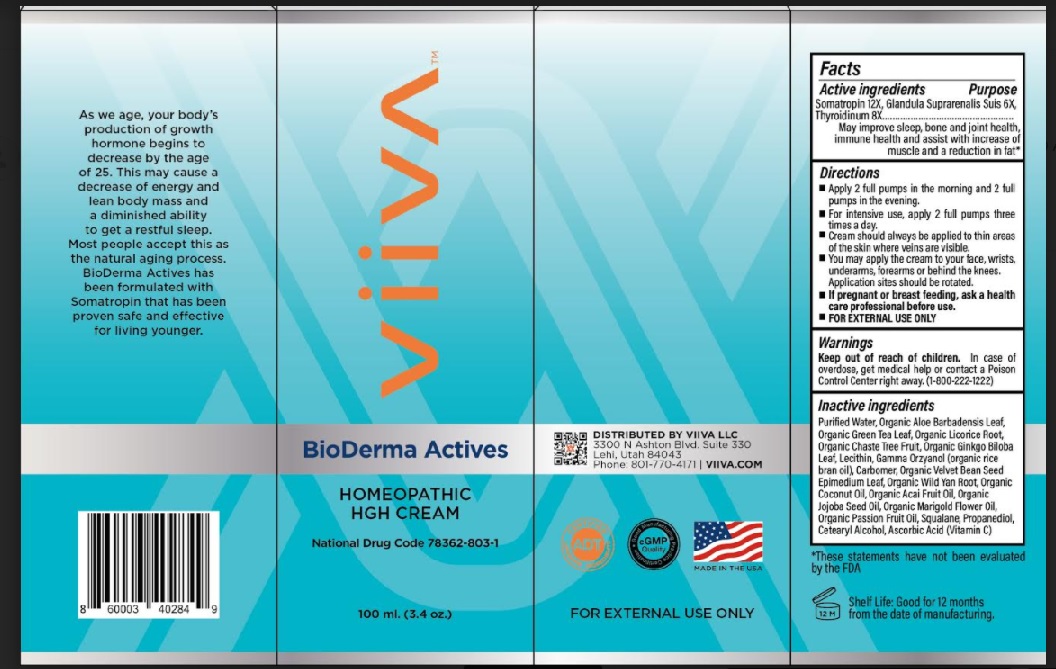 DRUG LABEL: VIIVA BioDerma Actives HGH Cream
NDC: 78362-803 | Form: CREAM
Manufacturer: Viiva LLC
Category: homeopathic | Type: HUMAN OTC DRUG LABEL
Date: 20210423

ACTIVE INGREDIENTS: SUS SCROFA ADRENAL GLAND 6 [hp_X]/1 g; THYROID, BOVINE 8 [hp_X]/1 g; SOMATROPIN 12 [hp_X]/1 g
INACTIVE INGREDIENTS: ALOE VERA LEAF; WATER; LICORICE; CHASTE TREE FRUIT; CARBOMER INTERPOLYMER TYPE A (ALLYL SUCROSE CROSSLINKED); GREEN TEA LEAF; GINKGO; GAMMA ORYZANOL; DIOSCOREA VILLOSA ROOT; ACAI OIL; TAGETES MINUTA FLOWER OIL; CETOSTEARYL ALCOHOL; ASCORBIC ACID; MUCUNA PRURIENS SEED; EPIMEDIUM SAGITTATUM TOP; COCONUT OIL; JOJOBA OIL; PASSIFLORA EDULIS FLOWER; PROPANEDIOL; SQUALANE

Active ingredients

SOMATROPIN 12X, Glandula suprarenalis suis 6X, Thyroidinum 8X

Purpose

May improve sleep, bone and joint health, immune health and assist with increase of muscle and a reduction in fat*

Directions

- Apply 2 full pumps in the morning and 2 full pumps in the evening.
- For intensive use, apply 2 full pumps three times a day.
- Cream should always be applied to thin areas of the skin where veins are visible.
- You may apply the cream to your face, wrists, underarms, forearms or behind the
  knees. Application sites should be rotated.
- If pregnant or breastfeeding, ask a health care professional before use.
- FOR EXTERNAL USE ONLY

Uses

As we age, your body's production of growth hormone beings to decrease by the age of
25. This may cause a decrease of energy and lean body mass and a diminished ability to
get a restful sleep. Most people accept this as the natural aging process. BioDerma
Actives has been formulated with Somatropin that has been proven safe and effective
for living younger. *
*These statements have not been evaluated by the FDA.

Warnings

In case of overdose or swallowed, get medical help or contact a Poison Control Center
right away (1-800-222-1222)

Inactive ingredients

Purified Water, Organic Aloe Barbadensis Leaf Extract, Organic Green Tea Leaf Extract,
Organic Licorice Root Extract, Organic Chaste Tree Fruit Extract, Organic Ginkgo Biloba
Leaf Extract, Lecithin, Gamma Orzyanol (organic rice bran oil), Carbomer, Organic Velvet
Bean Seed Epimedium Leaf Extract, Organic Wild Van Root Extract, Organic Coconut Oil,
Organic Acai Fruit Oil, Organic Jojoba Seed Oil, Organic Marigold Flower Oil, Organic
Passion Fruit Oil, Squalane, Propanediol, Cetearyl Alcohol, Ascorbic Acid (Vitamin C)